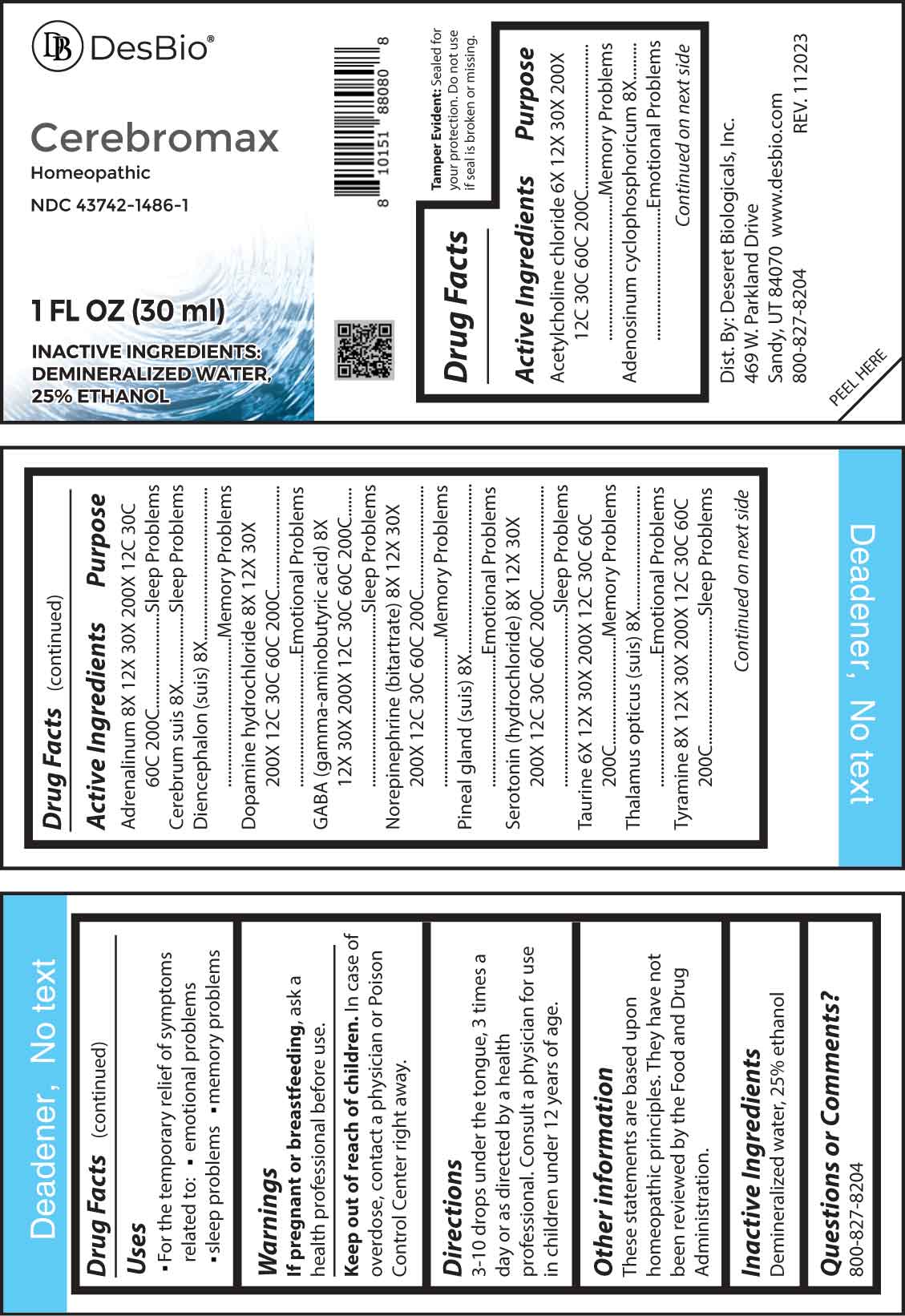 DRUG LABEL: Cerebromax
NDC: 43742-1486 | Form: LIQUID
Manufacturer: Deseret Biologicals, Inc.
Category: homeopathic | Type: HUMAN OTC DRUG LABEL
Date: 20240219

ACTIVE INGREDIENTS: ACETYLCHOLINE CHLORIDE 6 [hp_X]/1 mL; TAURINE 6 [hp_X]/1 mL; ADENOSINE CYCLIC PHOSPHATE 8 [hp_X]/1 mL; SUS SCROFA CEREBRUM 8 [hp_X]/1 mL; SUS SCROFA DIENCEPHALON 8 [hp_X]/1 mL; SUS SCROFA PINEAL GLAND 8 [hp_X]/1 mL; SUS SCROFA THALAMUS LATERAL GENICULATE NUCLEUS 8 [hp_X]/1 mL; EPINEPHRINE 8 [hp_X]/1 mL; DOPAMINE HYDROCHLORIDE 8 [hp_X]/1 mL; .GAMMA.-AMINOBUTYRIC ACID 8 [hp_X]/1 mL; NOREPINEPHRINE BITARTRATE 8 [hp_X]/1 mL; SEROTONIN HYDROCHLORIDE 8 [hp_X]/1 mL; TYRAMINE 8 [hp_X]/1 mL
INACTIVE INGREDIENTS: WATER; ALCOHOL

DRUG FACTS:

ACTIVE INGREDIENTS:

Acetylcholine Chloride 6X, 12X, 30X, 200X, 12C, 30C, 60C, 200C, Adenosinum Cyclophosphoricum 8X, Adrenalinum 8X, 12X, 30X, 200X, 12C, 30C, 60C, 200C, Cerebrum Suis 8X, Diencephalon (Suis) 8X, Dopamine Hydrochloride 8X, 12X, 30X, 200X, 12C, 30C, 60C, 200C, GABA (Gamma-Aminobutyric Acid) 8X, 12X, 30X, 200X, 12C, 30C, 60C, 200C, Norepinephrine (Bitartrate) 8X, 12X, 30X, 200X, 12C, 30C, 60C, 200C, Pineal Gland (Suis) 8X, Serotonin (Hydrochloride) 8X, 12X, 30X, 200X, 12C, 30C, 60C, 200C, Taurine 6X, 12X, 30X, 200X, 12C, 30C, 60C, 200C, Thalamus Opticus (Suis) 8X, Tyramine 8X, 12X, 30X, 200X, 12C, 30C, 60C, 200C.

PURPOSE:

Acetylcholine Chloride – Memory Problems, Adenosinum Cyclophosphoricum – Emotional Problems, Adrenalinum – Sleep Problems, Cerebrum Suis – Sleep Problems, Diencephalon (Suis) – Memory Problems, Dopamine Hydrochloride – Emotional Problems, GABA (Gamma-Aminobutyric Acid) – Sleep Problems, Norepinephrine (Bitartrate) – Memory Problems, Pineal Gland – Emotional Problems, Serotonin (Hydrochloride) – Sleep Problems, Taurine – Memory Problems, Thalamus Opticus (Suis) – Emotional Problems, Tyramine – Sleep Problems.

USES:

• For the temporary relief of symptoms related to:

• emotional problems • sleep problems • memory problems

These statements are based upon homeopathic principles. They have not been reviewed by the Food and Drug Administration.

WARNINGS:

If pregnant or breast-feeding, ask a health professional before use.

Keep out of reach of children. In case of overdose, contact a physician or Poison Control Center right away.

Tamper Evident: Sealed for your protection. Do not use if seal is broken or missing.

KEEP OUT OF REACH OF CHILDREN:

In case of overdose, contact a physician or Poison Control Center right away.

DIRECTIONS:

3-10 drops under the tongue, 3 times a day or as directed by a health professional. Consult a physician for use in children under 12 years of age.

INACTIVE INGREDIENTS:

Demineralized water, 25% ethanol

QUESTIONS:

Dist. By: Deseret Biologicals, Inc.

469 W. Parkland Drive

Sandy, UT 84070

www.desbio.com

800-827-8204

PACKAGE DISPLAY LABEL:

Des Bio

Cerebromax

Homeopathic

NDC 43742-1486-1

1 FL OZ (30 ml)